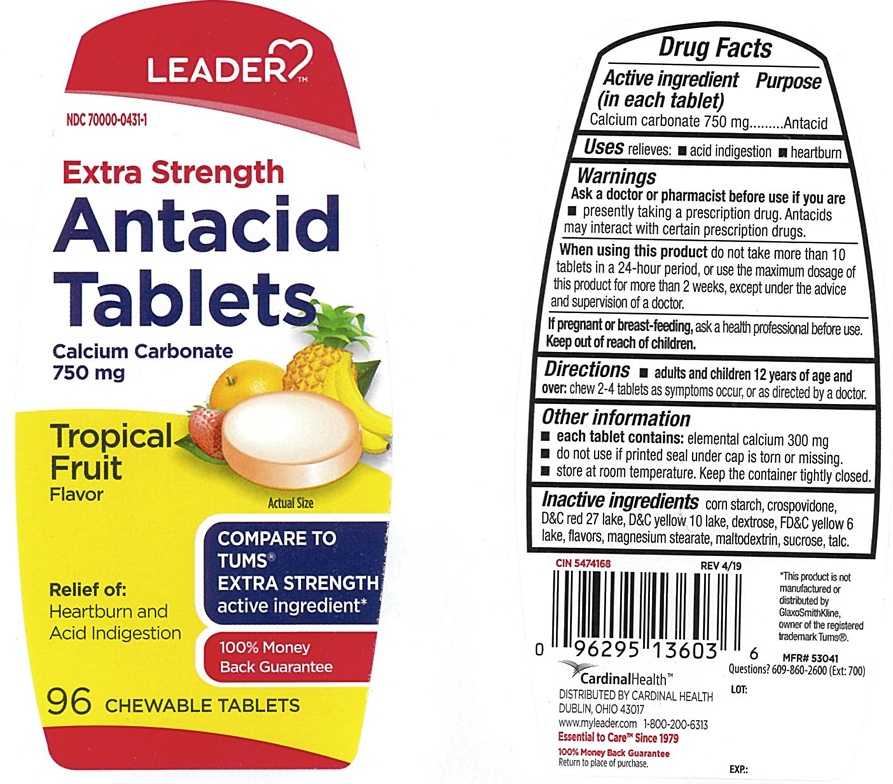 DRUG LABEL: Leader Extra Strength Antacid
NDC: 70000-0431 | Form: TABLET, CHEWABLE
Manufacturer: CARDINAL HEALTH 110, LLC. DBA LEADER
Category: otc | Type: Human OTC Drug Label
Date: 20250821

ACTIVE INGREDIENTS: CALCIUM CARBONATE 750 mg/1 1
INACTIVE INGREDIENTS: STARCH, CORN; CROSPOVIDONE; DEXTROSE, UNSPECIFIED FORM; MAGNESIUM STEARATE; MALTODEXTRIN; SUCROSE; TALC; D&C RED NO. 27; D&C YELLOW NO. 10; FD&C YELLOW NO. 6

Leader Extra Strength Antacid Tropical Fruit Chewable Tablets

ACTIVE INGREDIENT (in each tablet)

Calcium carbonate 750 mg

PURPOSE

Antacid

USE(S)

relieves:

- acid indigestion
- heartburn

WARNINGS

.

ASK A DOCTOR OR PHARMACIST BEFORE USE IF YOU ARE

- presently taking a prescription drug. Antacids may interact with certain prescription drugs.

WHEN USING THIS PRODUCT

do not take more than 10 tablets in a 24-hour period, or use the maximum dosage of this product for more than 2 weeks, except under the advice and supervision of a doctor.

IF PREGNANT OR/BREASTFEEDING,

ask a health professional before use.

KEEP OUT OF REACH OF CHILDREN

.

DIRECTIONS

- adults and children 12 years of age and over: chew 2-4 tablets as symptoms occur, or as directed by a doctor.

OTHER INFORMATION

- each tablet contains: elemental calcium 300 mg
- do not use if printed seal under cap is torn or missing.
- store at room temperature. Keep the container tightly closed.

INACTIVE INGREDIENTS

corn starch, crospovidone, D&C red 27 lake, D&C yellow 10 lake, dextrose, FD&C yellow 6 lake, flavors, magnesium stearate, maltodextrin, sucrose, talc.

PRINCIPAL DISPLAY PANEL

ADER
NDC 70000-0431-1
Extra Strength
Antacid Tablets
Calcium Carbonate 750 mg
Tropical Fruit Flavor
COMPARE TO TUMS® EXTRA STRENGTH active ingredient*
Relief of :

- Acid Indigestion
- Heartburn

96 CHEWABLE TABLETS